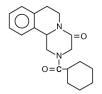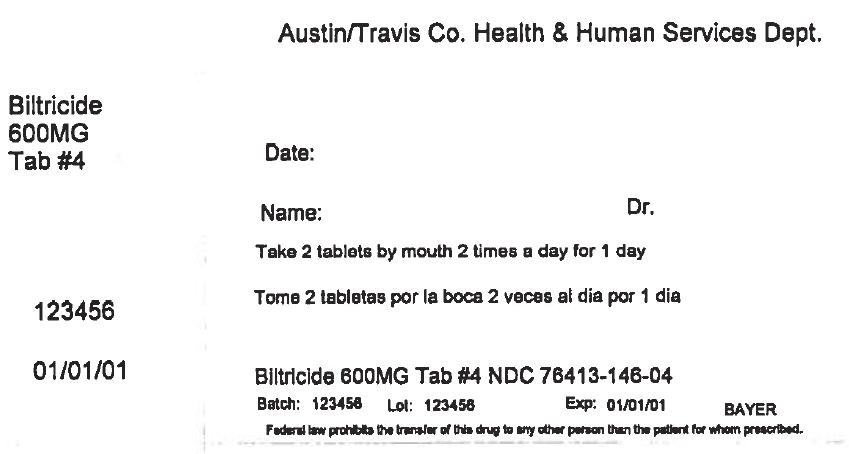 DRUG LABEL: Biltricide
NDC: 76413-146 | Form: TABLET, FILM COATED
Manufacturer: Central Texas Community Health Centers
Category: prescription | Type: HUMAN PRESCRIPTION DRUG LABEL
Date: 20170823

ACTIVE INGREDIENTS: PRAZIQUANTEL 600 mg/1 1
INACTIVE INGREDIENTS: STARCH, CORN; MAGNESIUM STEARATE; MICROCRYSTALLINE CELLULOSE; POVIDONE, UNSPECIFIED; SODIUM LAURYL SULFATE; POLYETHYLENE GLYCOL, UNSPECIFIED; TITANIUM DIOXIDE; HYPROMELLOSE, UNSPECIFIED

BILTRICIDE®
TABLETS
(praziquantel)

DESCRIPTION

BILTRICIDE® (praziquantel) is a trematodicide provided in tablet form for the oral treatment of schistosome infections and infections due to liver fluke.

BILTRICIDE (praziquantel) is 2-(cyclohexylcarbonyl)-1,2,3,6,7, 11b-hexahydro-4H-pyrazino [2, 1-a] isoquinolin-4-one with the molecular formula; C19H24N2O2. The structural formula is as follows:

Praziquantel is a white to nearly white crystalline powder of bitter taste. The compound is stable under normal conditions and melts at 136-140°C with decomposition. The active substance is hygroscopic. Praziquantel is easily soluble in chloroform and dimethylsulfoxide, soluble in ethanol and very slightly soluble in water.

BILTRICIDE tablets contain 600 mg of praziquantel. Inactive ingredients: corn starch, magnesium stearate, microcrystalline cellulose, povidone, sodium lauryl sulfate, polyethylene glycol, titanium dioxide and hypromellose.

CLINICAL PHARMACOLOGY

Praziquantel induces a rapid contraction of schistosomes by a specific effect on the permeability of the cell membrane. The drug further causes vacuolization and disintegration of the schistosome tegument.

After oral administration BILTRICIDE is rapidly absorbed (80%), subjected to a first pass effect, metabolized and eliminated by the kidneys. Maximal serum concentration is achieved 1-3 hours after dosing. The half-life of praziquantel in serum is 0.8-1.5 hours.

Special Populations

The pharmacokinetics of praziquantel were studied in 40 patients with Schistosoma mansoni infections with varying degrees of hepatic dysfunction (See table1). In patients with schistosomiasis, the pharmacokinetic parameters did not differ significantly between those with normal hepatic function (Group 1) and those with mild (Child-Pugh class A) hepatic impairment. However, in patients with moderate-to-severe hepatic dysfunction (Child-Pugh class B and C), praziquantel half-life, Cmax, and AUC increased progressively with the degree of hepatic impairment. In Child-Pugh class B, the increases in mean half-life, Cmax, and AUC relative to Group 1 were 1.58-fold, 1.76-fold, and 3.55-fold, respectively. The corresponding increases in Child-Pugh class C patients were 2.82-fold, 4.29-fold, and 15-fold for half-life, Cmax, and AUC.

Table 1: Pharmacokinetic parameters of praziquantel in four groups of patients with varying degrees of liver function following administration of 40 mg/kg under fasting conditions.
Patient Group | Half-life (hr) | Tmax (hr) | Cmax (µg/mL) | AUC (µg/mL* hr)
Normal hepatic function (Group 1) | 2.99 ± 1.28 | 1.48 ± 0.74 | 0.83 ± 0.52 | 3.02 ± 0.59
Child-Pugh A (Group 2) | 4.66 ± 2.77 | 1.37 ± 0.61 | 0.93 ± 0.58 | 3.87 ± 2.44
Child-Pugh B (Group 3) | 4.74 ± 2.16a | 2.21 ± 0.78a,b | 1.47 ± 0.74a,b | 10.72 ± 5.53a,b
Child-Pugh C (Group 4) | 8.45 ± 2.62a,b,c | 3.2 ± 1.05a,b,c | 3.57 ± 1.30a,b,c | 45.35 ± 17.50a,b,c
a) p<0.05 compared to Group 1
b) p<0.05 compared to Group 2
c) p<0.05 compared to Group 3

INDICATIONS AND USAGE

BILTRICIDE is indicated for the treatment of infections due to: all species of schistosoma (for example, Schistosoma mekongi, Schistosoma japonicum, Schistosoma mansoni and Schistosoma hematobium), and infections due to the liver flukes, Clonorchis sinensis/Opisthorchis viverrini (approval of this indication was based on studies in which the two species were not differentiated).

CONTRAINDICATIONS

BILTRICIDE is contraindicated in patients who previously have shown hypersensitivity to the drug or any of the excipients. Since parasite destruction within the eye may cause irreversible lesions, ocular cysticercosis must not be treated with this compound.

Concomitant administration with strong Cytochrome P450 (P450) inducers, such as rifampin, is contraindicated since therapeutically effective blood levels of praziquantel may not be achieved (see PRECAUTIONS/Drug Interactions). In patients receiving rifampin who need immediate treatment for schistosomiasis, alternative agents for schistosomiasis should be considered. However, if treatment with praziquantel is necessary, rifampin should be discontinued 4 weeks before administration of praziquantel. Treatment with rifampin can then be restarted one day after completion of praziquantel treatment (see PRECAUTIONS/Drug Interactions).

WARNINGS

Therapeutically effective levels of BILTRICIDE may not be achieved when administered concomitantly with strong P450 inducers, such as rifampin (see CONTRAINDICATIONS).

PRECAUTIONS

General

Approximately 80% of a dose of praziquantel is excreted in the kidneys, almost exclusively (>99%) in the form of metabolites. Excretion might be delayed in patients with impaired renal function, but accumulation of unchanged drug would not be expected. Therefore, dose adjustment for renal impairment is not considered necessary. Nephrotoxic effects of praziquantel or its metabolites are not known.

Caution should be exercised in the administration of the usual recommended dose of praziquantel to hepatosplenic schistosomiasis patients with moderate to severe liver impairment (Child-Pugh class B and C). Reduced metabolism of praziquantel by the liver in these patients may lead to considerably higher and longer lasting plasma concentrations of unmetabolized praziquantel (See CLINICAL PHARMACOLOGY/Special Populations).

Minimal increases in liver enzymes have been reported in some patients.

Patients suffering from cardiac irregularities should be monitored during treatment.

As BILTRICIDE can exacerbate central nervous system pathology due to schistosomiasis, as a general rule this drug should not be administered to individuals reporting a history of epilepsy and/or other signs of potential central nervous systems involvement such as subcutaneous nodules suggestive of cysticercosis.

When schistosomiasis or fluke infection is found to be associated with cerebral cysticercosis it is advised to hospitalize the patient for the duration of treatment.

Published in vitro data have shown a potential lack of efficacy of praziquantel against migrating schistosomulae. Data from two observational cohort studies in patients indicate that treatment with praziquantel in the acute phase of infection may not prevent progression from asymptomatic infection to acute schistosomiasis or from asymptomatic infection/ acute schistosomiasis into chronic phase.

In addition, the use of praziquantel in patients with schistosomiasis may be associated with clinical deterioration (paradoxical reactions, serum sickness Jarisch-Herxheimer like reactions: sudden inflammatory immune response suspected to be caused by the release of schistosomal antigens). These reactions predominantly occur in patients treated during the acute phase of schistosomiasis. They may lead to potentially life-threatening events, for example, respiratory failure, encephalopathy, and/or cerebral vasculitis.

Information for Patients

Patients should be warned not to drive a car and not to operate machinery on the day of BILTRICIDE treatment and the following day.

Drug Interactions

Concomitant administration of rifampin, a strong P450 inducer, with praziquantel is contraindicated and must be avoided (see CONTRAINDICATIONS). In a crossover study with a 2-week washout period, 10 healthy subjects ingested a single 40 mg/kg dose of praziquantel following pre-treatment with oral rifampin (600 mg daily for 5 days). Plasma praziquantel concentrations were undetectable in 7 out of 10 subjects. When a single 40 mg/kg dose of praziquantel was administered to these healthy subjects two weeks after discontinuation of rifampin, the mean praziquantel AUC and Cmax were 23% and 35% lower, respectively, than when praziquantel was given alone. In patients receiving rifampin, for example, as part of a combination regimen for the treatment of tuberculosis, alternative agents for schistosomiasis should be considered. However, if treatment with praziquantel is necessary, treatment with rifampin should be discontinued 4 weeks before administration of praziquantel. Treatment with rifampin can then be restarted one day after completion of praziquantel treatment.

Concomitant administration of other drugs that increase the activity of drug metabolizing liver enzymes (P450 inducers), for example, antiepileptic drugs (phenytoin, phenobarbital and carbamazepine), and dexamethasone, may also reduce plasma levels of praziquantel. Concomitant administration of drugs that decrease the activity of drug metabolizing liver enzymes (P 450 inhibitors), for example, cimetidine, ketoconazole, itraconazole, erythromycin may increase plasma levels of praziquantel.

Grapefruit juice was reported to produce a 1.6-fold increase in the Cmax and a 1.9-fold increase in the AUC of praziquantel. However, the effect of this exposure increase on the therapeutic effect and safety of praziquantel has not been systematically evaluated.

Mutagenesis, Carcinogenesis, Impairment of Fertility

Mutagenicity studies of praziquantel published in the scientific literature are inconclusive. Long term oral carcinogenicity studies in rats and golden hamsters did not reveal any carcinogenic effect at doses up to 250 mg/kg/day (about half of the human daily dose based on body surface area). Praziquantel had no effect on fertility and general reproductive performance of male and female rats when given at oral doses ranging from 30 to 300 mg/kg body weight (up to 0.65 times the human daily dose based on body surface area).

Pregnancy Category B

Developmental toxicity studies have been performed in rats and rabbits at dose levels of 30 to 300 mg/kg body weight given repeatedly during the period of organogenesis. No harm to the fetus due to praziquantel was observed. These doses were up to 0.65 times (rats) or 1.3 times (rabbits) the highest recommended human daily dose of 75 mg/kg/day, based on body surface area. There are, however, no adequate and well-controlled studies in pregnant women. While animal reproduction studies are not always predictive of human response, this drug should be used during pregnancy only if clearly needed.

Nursing mothers

Praziquantel appeared in the milk of nursing women at a concentration of about 1/4 that of maternal serum although it is not known, whether a pharmacological effect is likely to occur in children. Women should not nurse on the day of BILTRICIDE treatment and during the subsequent 72 hours.

Pediatric use

Safety in children under 4 years of age has not been established.

Geriatric use

Clinical studies of praziquantel did not include a sufficient number of subjects ages 65 and over to determine whether they respond differently from younger subjects. Other reported clinical experience has not identified differences in responses between the elderly and younger patients, but greater sensitivity of some older patients cannot be ruled out.

This drug is known to be substantially excreted by the kidney. Because elderly patients are more likely to have decreased renal function, the risk of toxic reactions to this drug may be greater in these patients.

ADVERSE EVENTS

The following side effects were observed generally in order of severity: malaise, headache, dizziness, abdominal discomfort with or without nausea, rise in temperature and urticaria. Such side effects may be more frequent and/or serious in patients with a heavy worm burden.

Post Marketing Adverse Event Reports

Additional adverse events reported from worldwide post marketing experience and from publications with praziquantel include: abdominal pain, allergic reaction (generalized hypersensitivity, including polyserositis), anorexia, arrhythmia (including bradycardia, ectopic rhythms, ventricular fibrillation, AV blocks), asthenia, bloody diarrhea, convulsion, eosinophilia, fatigue, myalgia, pruritus, rash, somnolence, vertigo and vomiting.

OVERDOSAGE

No data are available in humans.

DOSAGE AND ADMINISTRATION

The dosage recommended for the treatment of schistosomiasis is: 20 mg/kg bodyweight three times a day as a one day treatment, at intervals of not less than 4 hours and not more than 6 hours. The recommended dose for clonorchiasis and opisthorchiasis is: 25 mg/kg bodyweight three times a day as a one day treatment, at intervals of not less than 4 hours and not more than 6 hours. The tablets should be washed down unchewed with water during meals. Keeping the tablets or segments thereof in the mouth can reveal a bitter taste which can promote gagging or vomiting.

HOW SUPPLIED

BILTRICIDE is supplied as a 600 mg white to orange tinged, film-coated, oblong tablet with three scores. The tablet is coded with "BAYER" on one side and "LG" on the reverse side. When broken, each of the four segments contains 150 mg of active ingredient so that the dosage can be easily adjusted to the patient's bodyweight.

Segments are broken off by pressing the score (notch) with thumbnails. If 1/4 of a tablet is required, this is best achieved by breaking the segment from the outer end.

BILTRICIDE is available in bottles of 6 tablets.

Bottles of 6 | Strength 600 mg | NDC 50419-747-01
Store below 86°F (30°C).

Manufactured for:

Bayer HealthCare Pharmaceuticals Inc.
Whippany, NJ 07981
Manufactured in Germany

BILTRICIDE is a registered trademark of Bayer Aktiengesellschaft.

Rx Only

2/14

©2014 Bayer HealthCare Pharmaceuticals Inc. Printed in USA

PRINCIPAL DISPLAY PANEL - 600 MG Tablet Bottle Label

Austin/Travis Co. Health & Human Services Dept.

Biltricide
600MG
Tab #4

Date:

Name:
Dr.

Take 2 tablets by mouth 2 times a day for 1 day

123456

01/01/01

Biltricide 600MG Tab #4 NDC 76413-146-04

Batch: 123456
Lot: 123456
Exp: 01/01/01
BAYER

Federal law prohibits the transfer of this drug to any other person than the patient for whom prescribed.